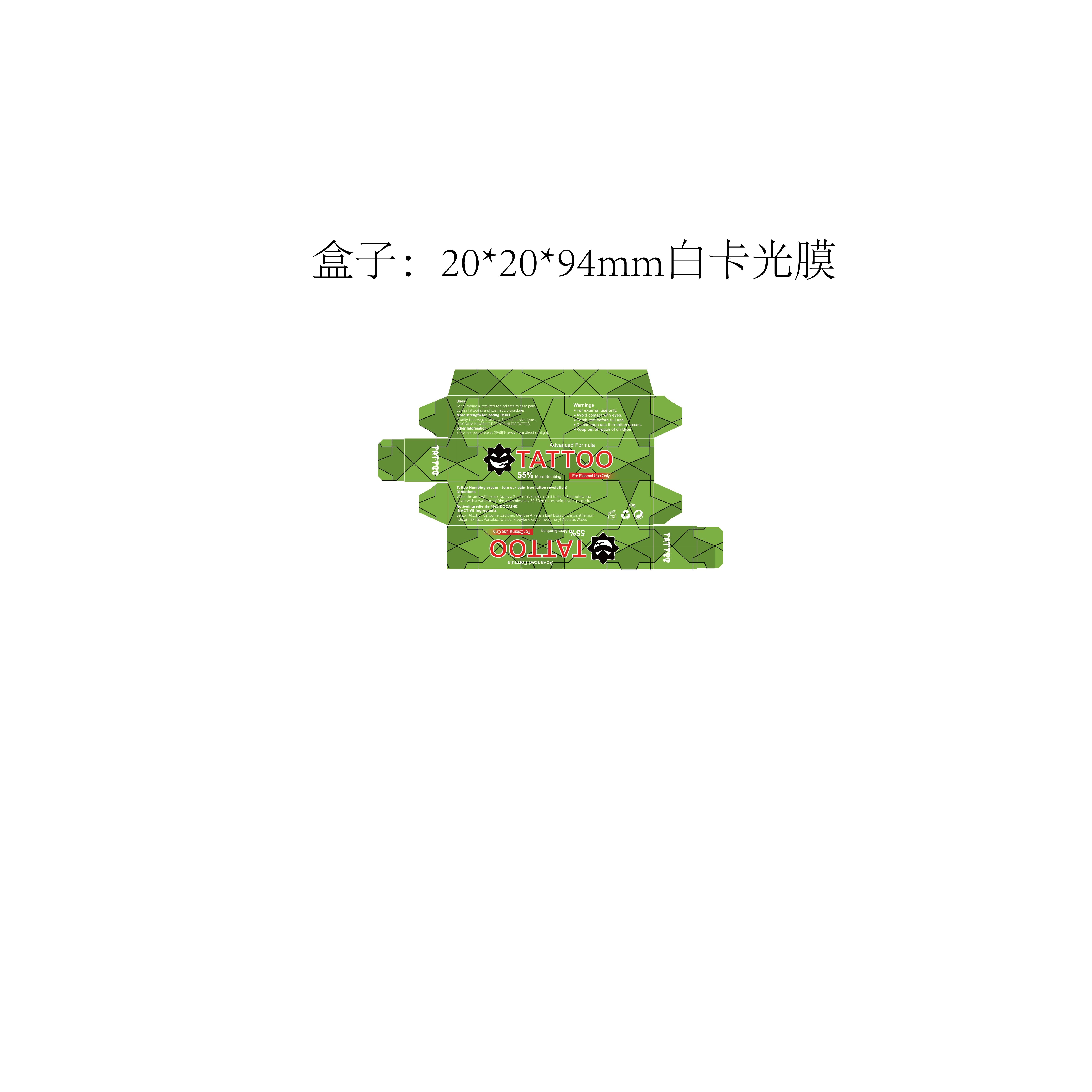 DRUG LABEL: 4% 10gTATTOO Numb Cream
NDC: 84019-031 | Form: CREAM
Manufacturer: Shengnan (Guangzhou) Cosmetics Co., LTD
Category: otc | Type: HUMAN OTC DRUG LABEL
Date: 20250407

ACTIVE INGREDIENTS: LIDOCAINE 100 mg/1 g
INACTIVE INGREDIENTS: CARBOMER; WATER; BENZYL ALCOHOL

WARNINGS

For external use only.Avoid contact with eyes.Patch test before full use.Patch test before full use.

PURPOSE

For numbing a localized topical area to ease painduring tattooing and cosmetic procedures.

Discontinue use if irritation occurs.

ACTIVE INGREDIENT

4% LIDOCAINE

WHEN USING

Wash the area with soap. Apply a 2 mm-thick layer, rub it in for 1-2 minutes, and
cover with a waterproof film approximately 30-50 minutes before your procedure.

INACTIVE INGREDIENT

Benzyl Alcohol, Carbomer, Lecithin,Mentha Arvensis Leaf Extract,chrysanthemum indicum Extract, Portulaca Oleracea Extract,Propylene Glycol, Tocopheryl Acetate, Water

DOSAGE AND ADMINISTRATION

Apply 1-3 times a week

INDICATIONS AND USAGE

Store in a cool place at 59-68°F, away from direct sunlight.